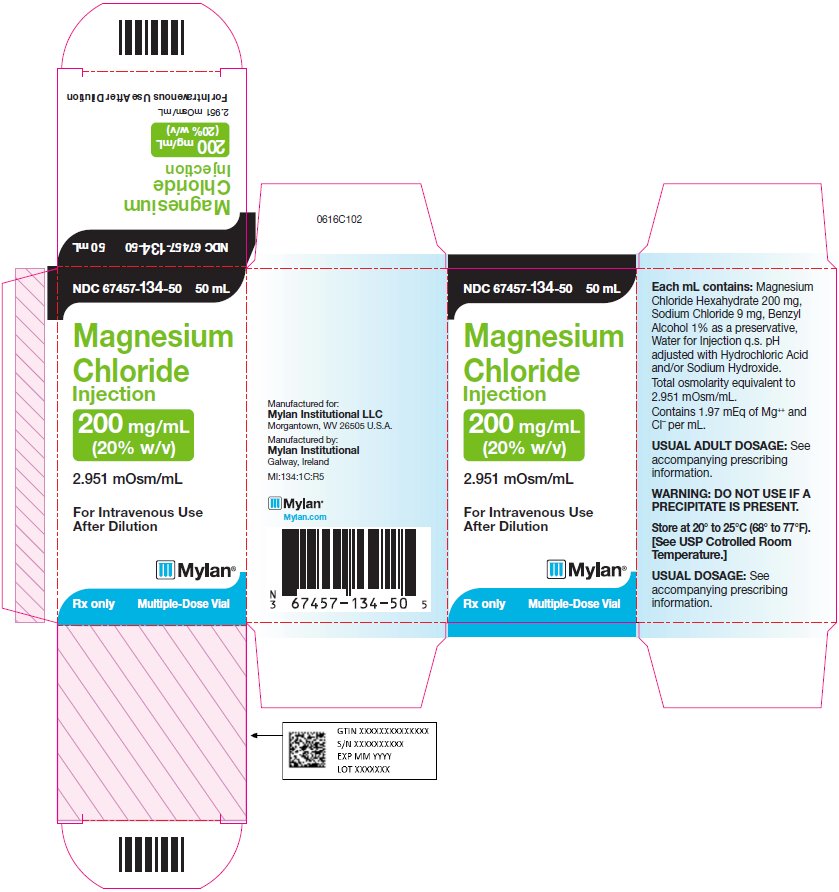 DRUG LABEL: Magnesium Chloride
NDC: 67457-134 | Form: INJECTION
Manufacturer: Mylan Institutional LLC
Category: prescription | Type: HUMAN PRESCRIPTION DRUG LABEL
Date: 20211015

ACTIVE INGREDIENTS: MAGNESIUM CHLORIDE 200 mg/1 mL
INACTIVE INGREDIENTS: SODIUM CHLORIDE 9 mg/1 mL; BENZYL ALCOHOL 10 mg/1 mL; WATER; HYDROCHLORIC ACID; SODIUM HYDROXIDE

DESCRIPTION

Magnesium Chloride Injection is a sterile solution of Magnesium Chloride Hexahydrate in Water for Injection q.s. Each mL contains Magnesium Chloride Hexahydrate 200 mg, Sodium Chloride 9 mg, Benzyl Alcohol 1% as a preservative, Water for Injection, q.s. pH adjusted with Hydrochloric Acid and/or Sodium Hydroxide. Total osmolarity equivalent to 2.951 mOsm/mL.

Contains 1.97 mEq of Mg^++ and Cl^- per mL.

The structural formula is MgCl2•6H2O

ACTIONS

Magnesium is the second most plentiful cation within cellular fluids. It is an important activator of many enzyme systems and deficits are accompanied by a variety of functional disturbances.

INDICATIONS

As an electrolyte replenisher in magnesium deficiencies.

CONTRAINDICATIONS

Magnesium Chloride Injection should not be administered if there is renal impairment, marked myocardial disease or to comatose patients.

WARNING

Do not use if a precipitate is present.

PRECAUTIONS

The usual precautions for parenteral administration should be observed. Administer with caution if flushing and sweating occurs. A preparation of a calcium salt should be readily available for intravenous injection to counteract potential serious signs of magnesium intoxication. As long as deep tendon reflexes are active it is probable that the patient will not develop respiratory paralysis. Respiration and blood pressure should be carefully observed during and after administration of Magnesium Chloride Injection.

Pregnancy

Animal reproduction studies have not been conducted with magnesium chloride. It is also not known whether magnesium chloride can cause fetal harm when administered to a pregnant woman or can affect reproduction capacity. Magnesium Chloride should be given to a pregnant woman only if clearly needed.

ADVERSE REACTIONS

Flushing, sweating, sharply lowered blood pressure, hypothermia, stupor and ultimately respiratory depression.

DOSAGE AND ADMINISTRATION

For intravenous infusion: 4 grams in 250 mL of 5% Dextrose Injection, at a rate not exceeding 3 mL per minute. Serum magnesium levels should serve as a guide to continued dosage.

USUAL DOSAGE RANGE

1 to 40 grams daily.

Parenteral drug products should be inspected visually for particulate matter and discoloration prior to administration whenever solution and container permit.

HOW SUPPLIED

Magnesium Chloride Injection 200 mg/mL (20% w/v).

NDC 67457-134-50
50 mL Multiple-Dose Vial. Individually boxed.

Store at 20° to 25°C (68° to 77°F). [See USP Controlled
Room Temperature.]

Manufactured for:
Mylan Institutional LLC
Morgantown, WV 26505

Manufactured by:
Mylan Institutional
Galway, Ireland

1084L101
Revised: 10/2021
MI:MAGNIJ:R4

PRINCIPAL DISPLAY PANEL - 200 mg/mL

NDC 67457-134-50 50 mL

Magnesium
Chloride
Injection

200 mg/mL
(20% w/v)

2.951 mOsm/mL

For Intravenous Use After
Dilution

Rx only Multiple-Dose Vial

Each mL contains: Magnesium
Chloride Hexahydrate 200 mg,
Sodium Chloride 9 mg, Benzyl
Alcohol 1% as a preservative,
Water for Injection q.s. pH adjusted
with Hydrochloric Acid and/or
Sodium Hydroxide.

Total osmolarity equivalent to
2.951 mOsm/mL.

Contains 1.97 mEq of Mg^++ and CI¯
per mL.

WARNING: DO NOT USE IF A
PRECIPITATE IS PRESENT.

Store at 20° to 25°C (68° to 77°F).
[See USP Controlled Room
Temperature.]

Usual Dosage: See accompanying
prescribing information.

Manufactured for:
Mylan Institutional LLC
Morgantown, WV 26505 U.S.A.

Manufactured by:
Mylan Institutional
Galway, Ireland

MI:134:1C:R5

Mylan.com